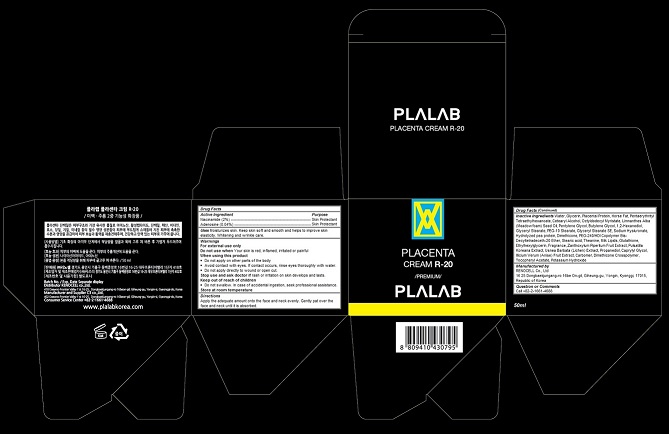 DRUG LABEL: Plalab Placenta R-20
NDC: 70326-103 | Form: CREAM
Manufacturer: RENOCELL Co., Ltd
Category: otc | Type: HUMAN OTC DRUG LABEL
Date: 20151223

ACTIVE INGREDIENTS: NIACINAMIDE 0.02 1/50 mL; ADENOSINE 0.0004 1/50 mL
INACTIVE INGREDIENTS: water; SUS SCROFA PLACENTA; Glycerin; Pentaerythrityl Tetraethylhexanoate; CETOSTEARYL ALCOHOL; Octyldodecyl Myristate; MEADOWFOAM SEED OIL; Pentylene Glycol; Butylene Glycol; 1,2-Hexanediol; GLYCERYL MONOSTEARATE; PEG-10 Stearate; Glyceryl Stearate SE; HYALURONATE SODIUM; HYDROLYZED SOY PROTEIN (ENZYMATIC; 2000 MW); Dimethicone; Stearic acid; Theanine; COW MILK FAT; Glutathione; Ethylhexylglycerin; ZANTHOXYLUM PIPERITUM FRUIT PULP; PULSATILLA KOREANA ROOT; USNEA BARBATA; Propanediol; Caprylyl Glycol; STAR ANISE FRUIT; CARBOXYPOLYMETHYLENE; DIMETHICONE CROSSPOLYMER (450000 MPA.S AT 12% IN CYCLOPENTASILOXANE); .ALPHA.-TOCOPHEROL ACETATE; POTASSIUM HYDROXIDE

Plalab Placenta Cream R-20